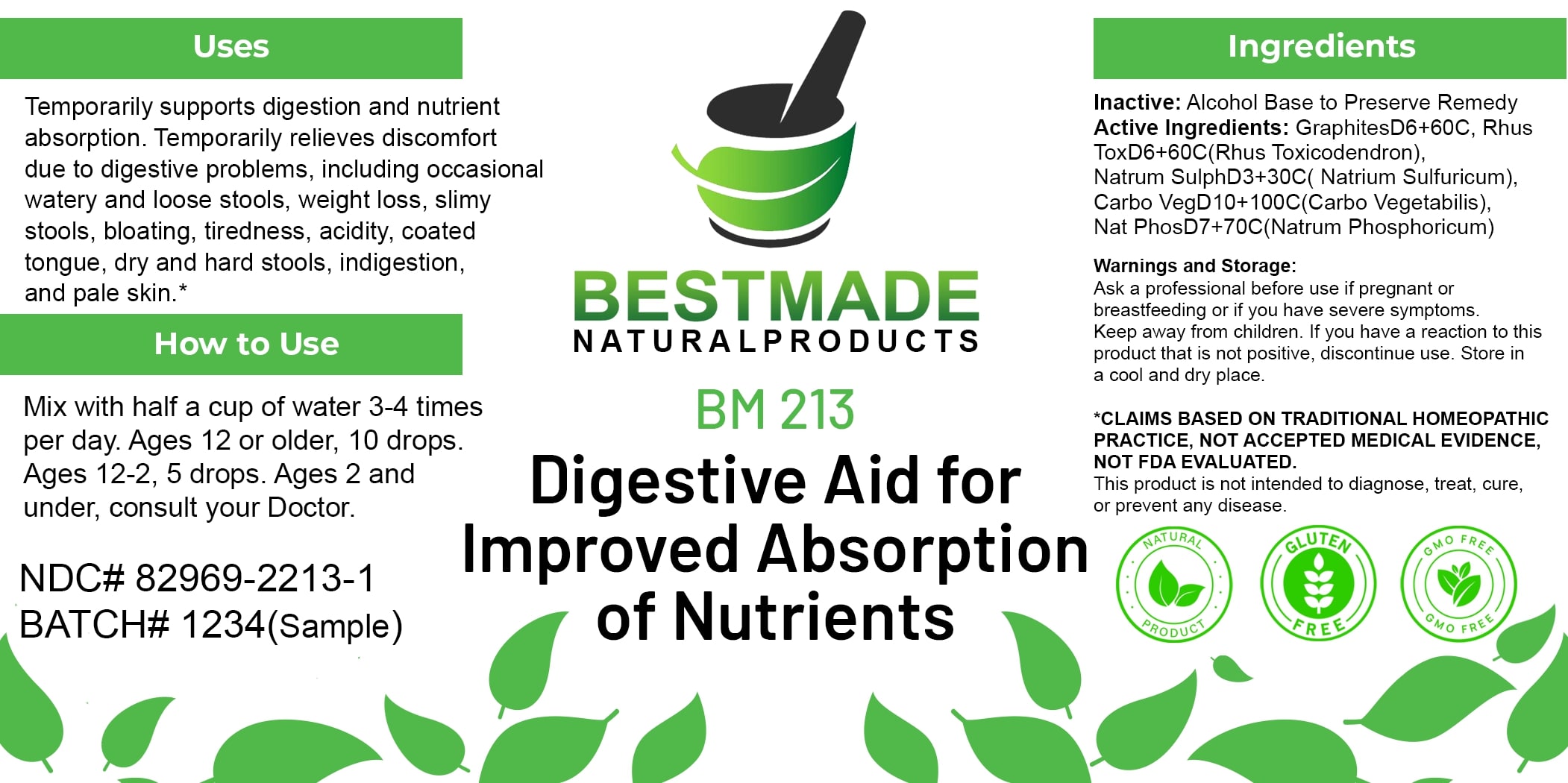 DRUG LABEL: Bestmade Natural Products BM213
NDC: 82969-2213 | Form: LIQUID
Manufacturer: Bestmade Natural Products
Category: homeopathic | Type: HUMAN OTC DRUG LABEL
Date: 20250303

ACTIVE INGREDIENTS: GRAPHITE 30 [hp_C]/30 [hp_C]; TOXICODENDRON PUBESCENS LEAF 30 [hp_C]/30 [hp_C]; ACTIVATED CHARCOAL 30 [hp_C]/30 [hp_C]; SODIUM SULFATE 30 [hp_C]/30 [hp_C]; SODIUM PHOSPHATE, DIBASIC, HEPTAHYDRATE 30 [hp_C]/30 [hp_C]
INACTIVE INGREDIENTS: ALCOHOL 30 [hp_C]/30 [hp_C]

BM213

DOSAGE AND ADMINISTRATION

How to Use

Mix with half a cup of water 3-4 times per day. Ages 12 or older, 10 drops. Ages 12-2, 5 drops. Ages 2 and under, consult your Doctor.

Uses

Temporarily supports digestion and nutrient absorption. Temporarily relieves discomfort due to digestive problems, including occasional watery and loose stools, weight loss, slimy stools, bloating, tiredness, acidity, coated tongue, dry and hard stools, indigestion, and pale skin.*

*CLAIMS BASED ON TRADITIONAL HOMEOPATHIC PRACTICE, NOT ACCEPTED MEDICAL EVIDENCE. NOT FDA EVALUATED.

This product is not intended to diagnose, treat, cure, or prevent any disease.

INACTIVE INGREDIENT

Ingredients

Inactive: Alcohol Base to Preserve Remedy

ACTIVE INGREDIENT

Active Ingredients: GraphitesD6+60C, Rhus ToxD6+60C(Rhus Toxicodendron), Natrum SulphD3+30C(Natrum Sulfuricum), Carbo VegD10+100C(Carbo Vegetabilis), Nat PhosD7+70C(Natrum Phosphoricum)

KEEP OUT OF REACH OF CHILDREN

Warnings and Storage:

Ask a professional before use if pregnant or breastfeeding or if you have severe symptoms. Keep away from children. If you have a reaction to this product that is not positive, discontinue use. Store in a cool and dry place.

Warnings and Storage:

Ask a professional before use if pregnant or breastfeeding or if you have severe symptoms. Keep away from children. If you have a reaction to this product that is not positive, discontinue use. Store in a cool and dry place.

*CLAIMS BASED ON TRADITIONAL HOMEOPATHIC PRACTICE, NOT ACCEPTED MEDICAL EVIDENCE. NOT FDA EVALUATED.

This product is not intended to diagnose, treat, cure, or prevent any disease.

Uses

Temporarily supports digestion and nutrient absorption. Temporarily relieves discomfort due to digestive problems, including occasional watery and loose stools, weight loss, slimy stools, bloating, tiredness, acidity, coated tongue, dry and hard stools, indigestion, and pale skin.*

*CLAIMS BASED ON TRADITIONAL HOMEOPATHIC PRACTICE, NOT ACCEPTED MEDICAL EVIDENCE. NOT FDA EVALUATED.

This product is not intended to diagnose, treat, cure, or prevent any disease.

Entire package label